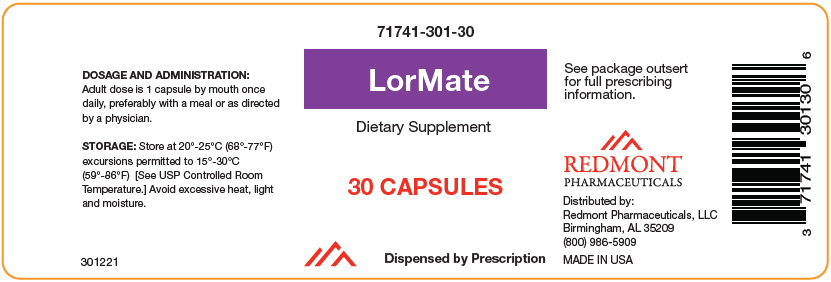 DRUG LABEL: LorMate
NDC: 71741-301 | Form: CAPSULE
Manufacturer: Redmont Pharmacetuicals, LLC
Category: other | Type: DIETARY SUPPLEMENT
Date: 20200504

ACTIVE INGREDIENTS: LEVOMEFOLATE CALCIUM 1 mg/1 1; Methylcobalamin 1 mg/1 1; Turmeric 500 mg/1 1
INACTIVE INGREDIENTS: Microcrystalline Cellulose 102; Silicon Dioxide; Magnesium Palmitostearate

LorMate

HEALTH CLAIM

71741-301-30
Dietary Supplement
Dispensed by Prescription

INDICATIONS

LorMate is an orally administered dietary supplement intended for the clinical dietary management of suboptimal nutritional status in patients taking methotrexate to treat their chronic inflammatory diseases where advanced folate, Vitamin B-12 supplementation and maintenance of good health is needed under physician supervision.

DIETARY SUPPLEMENT

LorMate has been formulated, manufactured and labeled in accordance with the requirements for Dietary Supplements. LorMate is to be used only under a physician's supervision.

Supplement Facts
Serving size: 1 Capsule
Serving per Container: 30
 | Amount per serving | Daily Value
Folate (as L-5-Methyltetrahydrofolic acid, Calcium salt) | 1 mg (1,670 mcg DFE) | 250%
Vitamin B-12 (as Methylcobalamin) | 1 mg | 16667%
CurcuGen™-Turmeric (Curcuma longa) (rhizome) Extract (standardized to 50% Total Curcuminoids) & Essential Oil (Oleoresin) Complex | 500 mg | [Daily Value not established]
Percent Daily Values are based on a 2,000 calorie diet. Your daily values may be higher or lower depending on your calorie needs.

DESCRIPTION

LorMate consists of a mixture of L-5-methyltetrahydrofolic acid, Calcium salt – 1mg, Vitamin B-12 as methylcobalamin – 1 mg, and CurcuGen™ Turmeric Extract and Essential Oil Complex – 500mg. L-5-methyltetrahydrofolate provides the methotrexate-induced distinctive nutritional requirement for folate due to competitive inhibition of reduced folate production in certain individuals who may have a more pronounced genetic polymorphism in the folate metabolic pathway. Methylcobalamin provides adequate Vitamin B-12 stores to avoid masking borderline deficiency Vitamin B-12 with external folate supplementation. Curcumin provides an increased nutritional requirement for antioxidants associated with methotrexate induced oxidative stress.

OTHER GRAS INGREDIENTS: Vegetable Cellulose (Capsule), Microcrystalline Cellulose, Silicon Dioxide, Magnesium Stearate.

All ingredients in LorMate are GRAS ingredients, approved food additives, or approved color additives.

Allergen: NONE

METHOTREXATE-INDUCED DISTINCT NUTRITIONAL REQUIREMENTS

Methotrexate is the most widely used disease modifying drug in the treatment of inflammatory diseases such as rheumatoid arthritis, psoriatic arthritis or psoriasis. Despite its therapeutic benefit as many as 30% of patients discontinue or reduce their dose due to its adverse effects caused by the failure to compensate for the increased need for folate acid. The increased requirement for folate results from the methotrexate induced reduction in the folate-mediated one-carbon metabolic pathway and other enzymatic processes for which reduced folate is a cofactor.

Methylcobalamin provides adequate Vitamin B-12 stores to avoid masking borderline deficiency of Vitamin B-12 with exogenous folate supplementation.

Methotrexate adverse events are thought to be caused by a disruption of cellular redox homeostasis (severe oxidative stress) with depletion of natural antioxidant mechanisms and marked rise in oxidative by-products. This creates increased nutritional requirement for supplemental dietary antioxidants (curcuminoids) thus reducing oxidative burden.

CLINICAL PHARMACOLOGY

PHARMACOKINETICS

L-5-methyltetrahydrofolate, the bioactive form of folate is well absorbed and able to participate in all biochemical processes for which folate is a cofactor.

Cobalamin

Cobalamin (Vitamin B-12) is well absorbed under normal conditions. However, geriatrics and individuals with reduced stomach acid production may inadequately absorb cobalamin. This defect can be corrected with administration of supplemental dietary Vitamin B-12. Individuals with autoimmune atrophic gastritis should be administered supplemental parenteral Vitamin B-12.

Mechanism of Action

L-5-methyltetrahydrofolate

Folic acid and its derivatives address the unique nutritional requirement for folic acid of patients using methotrexate to treat certain inflammatory diseases including rheumatoid arthritis, psoriatic arthritis or psoriasis. Folic acid and its derivatives are essential for the synthesis of DNA, the modification of DNA and RNA, the synthesis of methionine from homocysteine, serine and various other chemical reactions involved in cellular metabolism. These reactions are important in the metabolism and biosynthesis of amino acids, nucleic acids, membrane lipids, cholesterol and neurotransmitters. These reactions are collectively known as folate-mediated one-carbon metabolism. A significant proportion of the general population, however, has one or another polymorphism (genetic variation) in the folic acid metabolic pathway. Supplementing the folic acid metabolic pathway with L-5-methyltetrahydrofolate salts therefore may obviate or reduce the effect of these polymorphisms

Methylcobalamin

Methylcobalamin is an essential cofactor in many folate dependent metabolic pathways. Minor deficiencies in cobalamin levels may be obscured in the presence of greater than normal folate levels. Although this may suppress such clinical signs as megaloblastic anemia, it does not prevent neurological damage associated with Vitamin B-12 deficiency. Cobalamin supplementation provides sufficient Vitamin B-12 to assure that L-5-methyltetrahydrofolate administration does not mask cobalamin deficiency.

Curcuminoids

The pharmacological actions of curcumin have been studied by various researchers worldwide. Curcumin has the ability to suppress acute and chronic inflammation. It reduces inflammation by lowering histamine levels and by possibly increasing the production of natural cortisone by adrenal glands. In in vitro studies of curcumin demonstrated anti-inflammatory action on human vascular cells. The mechanism of action of curcumin anti-inflammatory effect is by attenuating inflammatory response of TNF-α stimulated human endothelial cells by interfering with NF-κB. Additionally curcumin is capable of preventing platelet-derived growth factor (PDGF).

TOXICITY

L-5-methyltetrahydrofolate

No toxicity issues have been reported from folate supplementation. However, folic acid alone is improper therapy in the treatment of pernicious anemia and other megaloblastic anemias where Vitamin B-12 is deficient. Folic acid in doses above 0.1 mg daily may obscure pernicious anemia in that hematologic remission can occur while neurological manifestations progress.

Methylcobalamin

No safety issues related to cobalamin supplementation have been reported.

Curcuminoids

No significant curcumin toxicity has been reported. Acute doses up to 12 gm and chronic doses of 10 gm/d have been found to be safe. Although dozens of human clinical trials have consistently demonstrated the lack of toxicity from curcumin, minor gastrointestinal complaints have occasionally been noted in these trials. A few in vitro studies suggest that curcumin may interfere with platelet aggregation.

CONTRAINDICATIONS

LorMate is contraindicated in patients with a known hypersensitivity to any of the ingredients.

WARNINGS

Folate may interfere with absorption of certain medications. Patients receiving both LorMate and tetracycline should take these medications at least one hour apart. The serum levels and the utilization of folate may be reduced when taken with sulfasalazine, phenytoin, statins and some birth control medications.

PRECAUTIONS

LorMate should only be used under the direction and supervision of a licensed medical practitioner.

LorMate use should be under the supervision of a physician when administered to patients that may have a medical condition, are pregnant, lactating, trying to conceive, under the age of 18, or taking other medications.

Folic acid alone is improper therapy in the treatment of pernicious anemia and other megaloblastic anemias where Vitamin B-12 is deficient. Folic acid in doses above 0.1 mg daily may obscure pernicious anemia in that hematologic remission can occur while neurological manifestations progress.

SPECIAL POPULATIONS

PREGNANCY AND LACTATION

LorMate use in pregnant or lactating patients should occur under the supervision of a patient's physician.

PEDIATRICS

Use of LorMate in pediatric populations should be under the supervision of a physician.

ADVERSE REACTIONS

You should call your doctor for medical advice about serious adverse events. To report adverse side effects or to obtain product information, contact Redmont Pharmaceuticals, LLC at 1-800-986-5909.

DOSAGE AND ADMINISTRATION

Adult dose is 1 capsule by mouth once daily, preferably with a meal or as directed by a physician.

HOW SUPPLIED

Bottles of 30 capsules (71741-301-30 [Redmont Pharmaceuticals does not represent this product code to be National Drug Code (NDC). Product code is formatted according to standard industry practice, to meet the formatting requirement by pedigree reporting and supply-chain control including pharmacies.]).
LorMate is supplied as a yellowish powder in a clear transparent capsule.

STORAGE

Store at 20°-25° C (68°-77°F) excursions permitted to 15°-30°C (59°-86°F) [See USP Controlled Room Temperature.] Avoid excessive heat, light and moisture.

HEALTH CLAIM

This product is a prescription-folate with or without other dietary ingredients that – due to increased folate levels increased risk associated with masking Vitamin B-12 deficiency (pernicious anemia) requires administration under the care of a licensed medical practitioner (64 FR 8760). 1-3 The most appropriate way to ensure pedigree reporting consistent with these regulatory guidelines and safety monitoring is to dispense this product only by prescription. This is not an Orange Book product. This product may be administered only under a physician's supervision and all prescriptions using this product shall be pursuant to state statues as applicable. The ingredients, indication or claims of this product are not to be construed to be drug claims.

1. Federal Register Notice of August 2, 1973 (38 FR 20750)
2. Federal Register Notice of October 17, 1980 (45 FR 69043, 69044)
3. Federal Register Notice of March 5, 1996 (61 FR 8760)

TAMPER EVIDENT: Do not use if seal is broken or missing.

MADE IN USA

Distributed by:
Redmont Pharmaceuticals, LLC
Birmingham, AL 35209
800-986-5909

CurcuGen™ is a registered trademark of Dolcas BioTech LLC
CurcuGen™ Turmeric Extract - Patents Pending

These statements have not been evaluated by the Food and Drug Administration. This product is not intended to diagnose, treat, cure, or prevent any disease.

KEEP THIS AND ALL MEDICATIONS OUT OF THE REACH OF CHILDREN.

301321

PRINCIPAL DISPLAY PANEL - 30 Capsule Bottle Label

71741-301-30

LorMate

Dietary Supplement

30 CAPSULES

Dispensed by Prescription